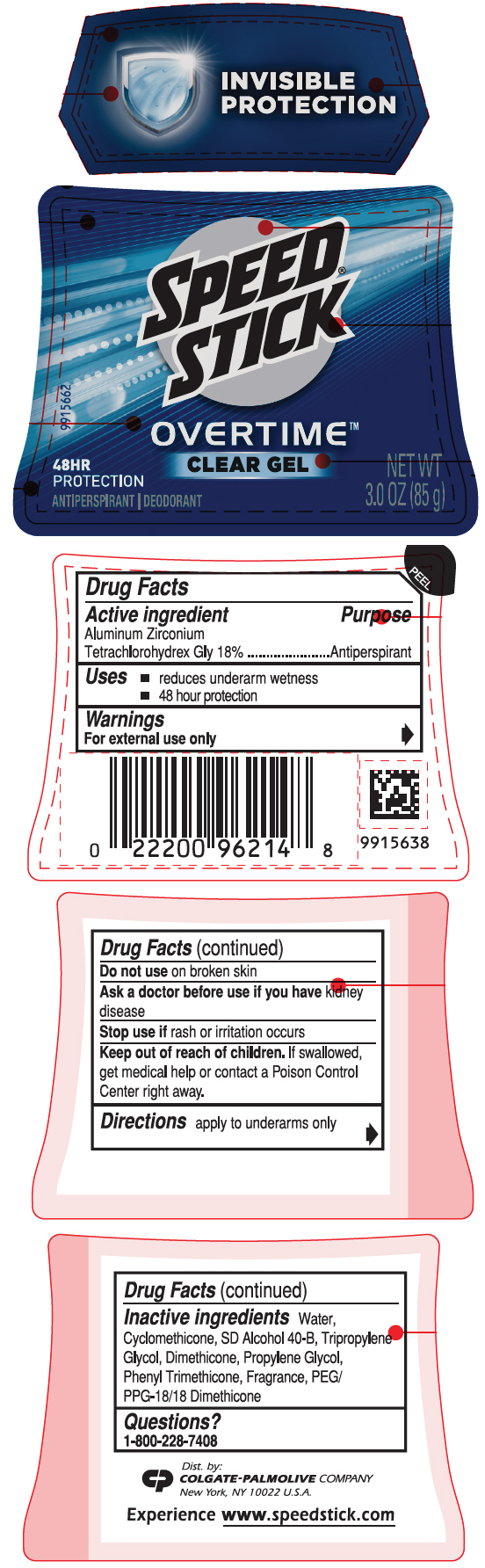 DRUG LABEL: Speed Stick Overtime Clear Gel
NDC: 35000-863 | Form: STICK
Manufacturer: COLGATE PALMOLIVE COMPANY
Category: otc | Type: HUMAN OTC DRUG LABEL
Date: 20200214

ACTIVE INGREDIENTS: ALUMINUM ZIRCONIUM TETRACHLOROHYDREX GLY 180 mg/1 g
INACTIVE INGREDIENTS: WATER; CYCLOMETHICONE; ALCOHOL; TRIPROPYLENE GLYCOL; DIMETHICONE; PROPYLENE GLYCOL; PHENYL TRIMETHICONE; PEG/PPG-18/18 DIMETHICONE

Speed® Stick Overtime™ Clear Gel

Drug Facts

Active ingredient

Aluminum Zirconium Tetrachlorohydrex Gly 18%

Purpose

Antiperspirant

Uses

- reduces underarm wetness
- 48 hour protection

Warnings

For external use only

Do not use on broken skin

Ask a doctor before use if you have kidney disease

Stop use if rash or irritation occurs

Keep out of reach of children. If swallowed, get medical help or contact a Poison Control Center right away.

Directions

apply to underarms only

Inactive ingredients

Water, Cyclomethicone, SD Alcohol 40-B, Tripropylene Glycol, Dimethicone, Propylene Glycol, Phenyl Trimethicone, Fragrance, PEG/PPG-18/18 Dimethicone

Questions?

1-800-228-7408

Dist. by:
COLGATE-PALMOLIVE COMPANY
New York, NY 10022 U.S.A.

PRINCIPAL DISPLAY PANEL - 85 g Container Label

INVISIBLE
PROTECTION

SPEED®
STICK

OVERTIME™
CLEAR GEL

48HR
PROTECTION

ANTIPERSPIRANT | DEODORANT

NET WT
3.0 OZ (85 g)

9915662